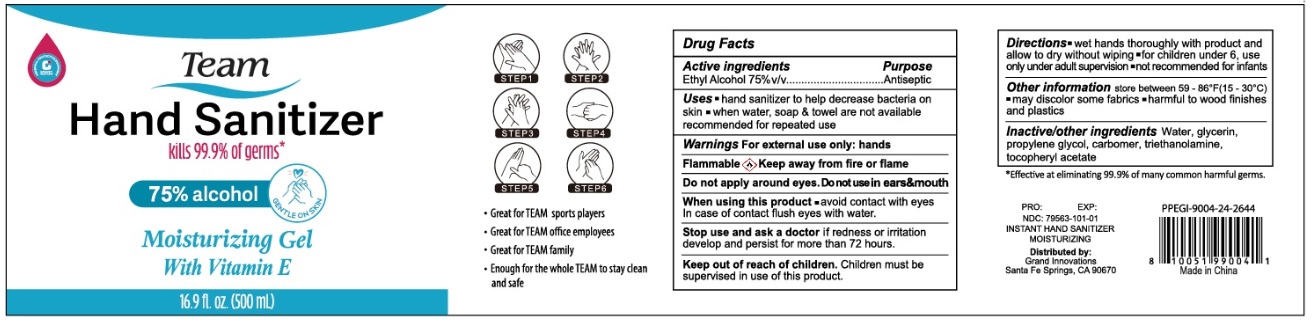 DRUG LABEL: Team Hand Sanitizer
NDC: 79563-101 | Form: GEL
Manufacturer: Vf & Co. Llc
Category: otc | Type: HUMAN OTC DRUG LABEL
Date: 20200717

ACTIVE INGREDIENTS: ALCOHOL 75 mL/100 mL
INACTIVE INGREDIENTS: WATER; GLYCERIN; PROPYLENE GLYCOL; CARBOMER HOMOPOLYMER, UNSPECIFIED TYPE; TROLAMINE; .ALPHA.-TOCOPHEROL ACETATE

Team Hand Sanitizer

Active ingredients

Ethyl Alcohol 75% v/v

Purpose

Antiseptic

INDICATIONS AND USAGE

Uses • hand sanitizer to help decrease bacteria on skin • when water, soap & towel not available recommended for repeated use

Warnings For external use only: hands

Flammable Keep away from fire or flame

Do not apply around eyes. Do not use in ears & mouth

When using this product • avoid contact with eyes. In case of contact flush eyes with water.

Stop use and ask a doctor if redness or irritation develop and persist for more than 72 hours.

Keep out of reach of children. Children must be supervised in use of this product.

DOSAGE AND ADMINISTRATION

Directions • wet hands thoroughly with product and allow to dry without wiping • for children under 6, use only under adult supervision • not recommended for infants

Other information store between 59 - 86°F (15 - 30°C) • may discolor some fabrics • harmful to wood finishes and plastics

INACTIVE INGREDIENT

Inactive/other ingredients Water, Glycerine, propylene glycol, carbomer, triethanolamine, tocopheryl acetate

kills 99.9% of germs*

75% alcohol

Moisturizing Gel With Vitamin E

• Great for TEAM sports players

• Great for TEAM office employees

• Great for TEAM family

• Enough for the whole TEAM to stay clean and safe

*Effective at eliminating 99.9% of many common harmful germs.

INSTANT HAND SANITIZER MOISTURIZING

Distributed by:
Grand Innovations
Santa Fe Springs, CA 90670

Made in China